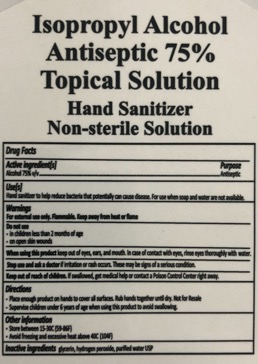 DRUG LABEL: Hand Sanitizer
NDC: 73874-0001 | Form: LIQUID
Manufacturer: Elevation Gourmet, Inc.
Category: otc | Type: HUMAN OTC DRUG LABEL
Date: 20200327

ACTIVE INGREDIENTS: ALCOHOL 75 mL/100 mL
INACTIVE INGREDIENTS: GLYCEROL FORMAL 1.45 mL/100 mL; HYDROGEN PEROXIDE 0.125 mL/100 mL; WATER 23.425 mL/100 mL

Active Ingredients & Label

Active Ingredient(s)

Isopropyl alcohol 75% v/v........Antiseptic

Purpose & Use

Use(s)

Hand sanitizer to help reduce bacteria that potentially can cause disease. For use when soap and water are not available.

Warnings

For external use only. Flammable. Keep away from heat or flame.

Do Not Use

-In children less than 2 months of age

-On open skin wounds

When Using

When using this product keep out of eyes, ears, and mouth. In case of contact with eyes, rinse eyes thoroughly with water.

Stop Use

Stop use and ask a doctor if irritation or rash occurs. These may be signs of a serious condition.

Keep out of reach of children. If swallowed, get medical help or contact a PoisonControl Center right away.

Instructions for use

Directions

-Place enough product on hands to cover all surfaces. Rub hands together until dry. Not for Resale.

-Supervise children under 6 years of age when using this product to avoid swallowing.

Other information

-Store between 15-30C (59-86F)

-Avoid freezing and excessive heat above 40C (104F)

Inactive Ingredients

Inactive Ingredients glycerin, hydrogen peroxide, purified water USP

Directions

-Place enough product on hands to cover all surfaces. Rub hands together until dry. Not for Resale.

-Supervise children under 6 years of age when using this product to avoid swallowing.

Uses and Directions

Use(s)

Hand sanitizer to help reduce bacteria that potentially can cause disease. For use when soap and water are not available.

Directions

-Place enough product on hands to cover all surfaces. Rub hands together until dry. Not for resale.

Supervise children under 6 years of age when using this product to avoid swallowing.